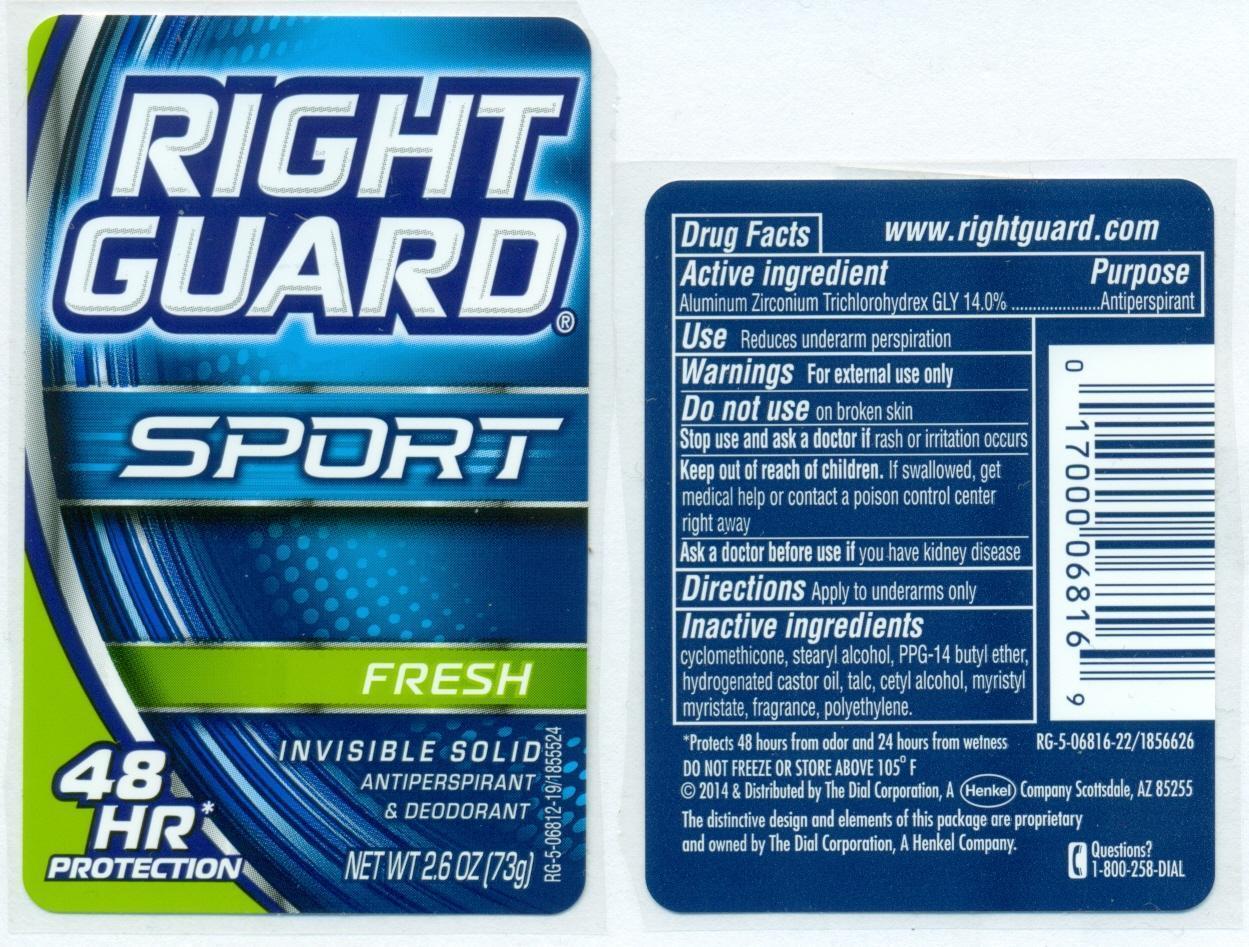 DRUG LABEL: Right Guard Sport Fresh Invisible Solid Antiperspirant and Deodorant
NDC: 54340-233 | Form: STICK
Manufacturer: The Dial Corporation
Category: otc | Type: HUMAN OTC DRUG LABEL
Date: 20140130

ACTIVE INGREDIENTS: Aluminum Zirconium Trichlorohydrex Gly 14.00 g/73 g
INACTIVE INGREDIENTS: CYCLOMETHICONE 5 23.66 g/73 g; STEARYL ALCOHOL 15.41 g/73 g; PPG-14 BUTYL ETHER 10.22 g/73 g; HYDROGENATED CASTOR OIL 3.53 g/73 g; MYRISTYL MYRISTATE 1.40 g/73 g; TALC 2.79 g/73 g; CETYL ALCOHOL 1.75 g/73 g

Right Guard Sport Fresh Invisible Solid Antiperspirant and Deodorant

ACTIVE INGREDIENT

Aluminum Zirconium Trichlorohydrex Gly 14.0%

PURPOSE

Antiperspirant

INDICATIONS AND USAGE

Use: Reduces underarm perspiration

Warnings: For external use only.

Do not use on broken skin.

Stop use and ask a doctor if rash or irritation occurs.

Keep out of reach of children. If swallowed, get medical help or contact a poison control center right away.

Ask a doctor before use if you have kidney disease.

DOSAGE AND ADMINISTRATION

Directions: Apply to underarms only.

INACTIVE INGREDIENT

Cyclomethicone, stearyl alcohol, PPG-14 butyl ether, hydrogenated castor oil, talc, cetyl nalcohol, myristyl myristate, fragrance, polyethylene.

STORAGE AND HANDLING

DO NOT FREEZE OR STORE ABOVE 105°F

HOW SUPPLIED

2012 Distributed by The Dial Corporation A Henkel Company Scottsdale, AZ, 85255. The distinctive design and elements of this package are proprietary and owned by the Dial Corporation, a Henkel Company. U.S.PAT.NO.:5,417,964

Questions? 1-800-258-DIAL